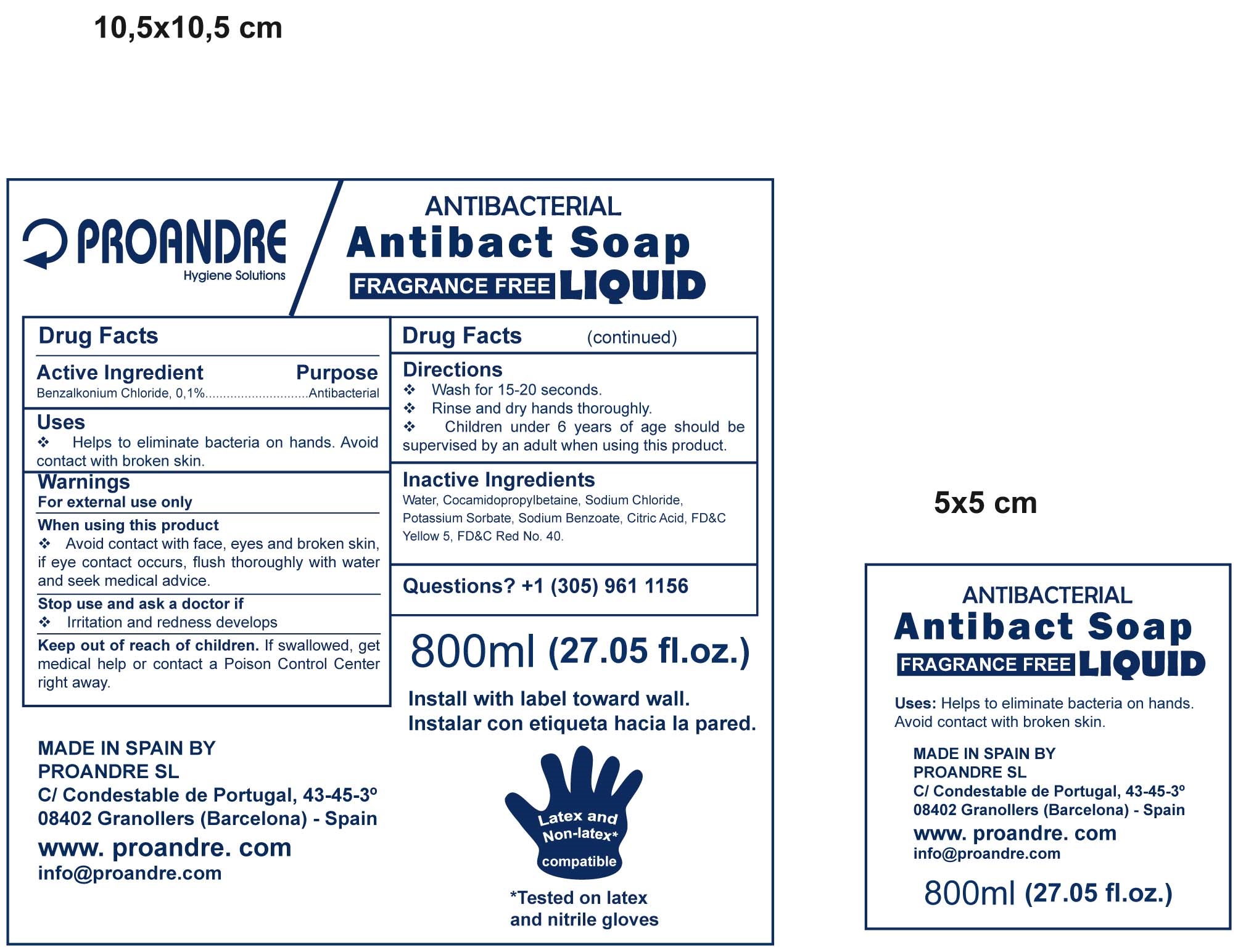 DRUG LABEL: Proandre
NDC: 70028-002 | Form: LIQUID
Manufacturer: PROANDRE, SL
Category: otc | Type: HUMAN OTC DRUG LABEL
Date: 20161125

ACTIVE INGREDIENTS: BENZALKONIUM CHLORIDE 0.1 mg/1 mL
INACTIVE INGREDIENTS: WATER 80.079 mg/1 mL; COCAMIDOPROPYL BETAINE 18.1 mg/1 mL; SODIUM CHLORIDE 0.9 mg/1 mL; POTASSIUM SORBATE 0.3 mg/1 mL; SODIUM BENZOATE 0.3 mg/1 mL; ANHYDROUS CITRIC ACID 0.02 mg/1 mL; FD&C YELLOW NO. 5 0.0005 mg/1 mL; FD&C RED NO. 40 0.0005 mg/1 mL

Active Ingredient Purpose

Benzalkonium Chloride 0.1%....................Antibacterial

Uses

* Helps to eliminate bacteria on hands. Avoid

contact with broken skin

Directions

* Wash for 15-20 seconds

* Rinse and dry hands thoroughly.

* Children under 6 years of age should be

supervised by an adult when using this product

Uses

* Helps to eliminate bacteria on hands. Avoid

contact with broken skin

WARNINGS

For External Use only

When using this product:

* Avoid contact with face, eyes and broken skin

if eyes contact occurs, flush thoroughly with water

and seek medical advice.

WARNINGS

For External Use only

When using this product:

* Avoid contact with face, eyes and broken skin

if eyes contact occurs, flush thoroughly with water

and seek medical advice.

Stop use and ask doctor if

* Irritation and redness develops.

Keep Out of reach of children

If swallowed, get medical help or

contact a Poison Control Center

right away.

Questions?.

+ 1 (305) 961 1156

Dossage and Administration

* Wash for 15-20 seconds

* Rinse and dry hands thoroughly.

* Children under 6 years of age should be

supervised by an adult when using this product

Inactive ingredients

Water, Cocamidopropylbetaine, sodium chloride,

potassium sorbate, sodium benzoate, citric acid,

FD&C Yellow 5, FD&C Red 40.

ANTIBACTERIAL ANTIBACT SOAP LIQUID

Fragrance free